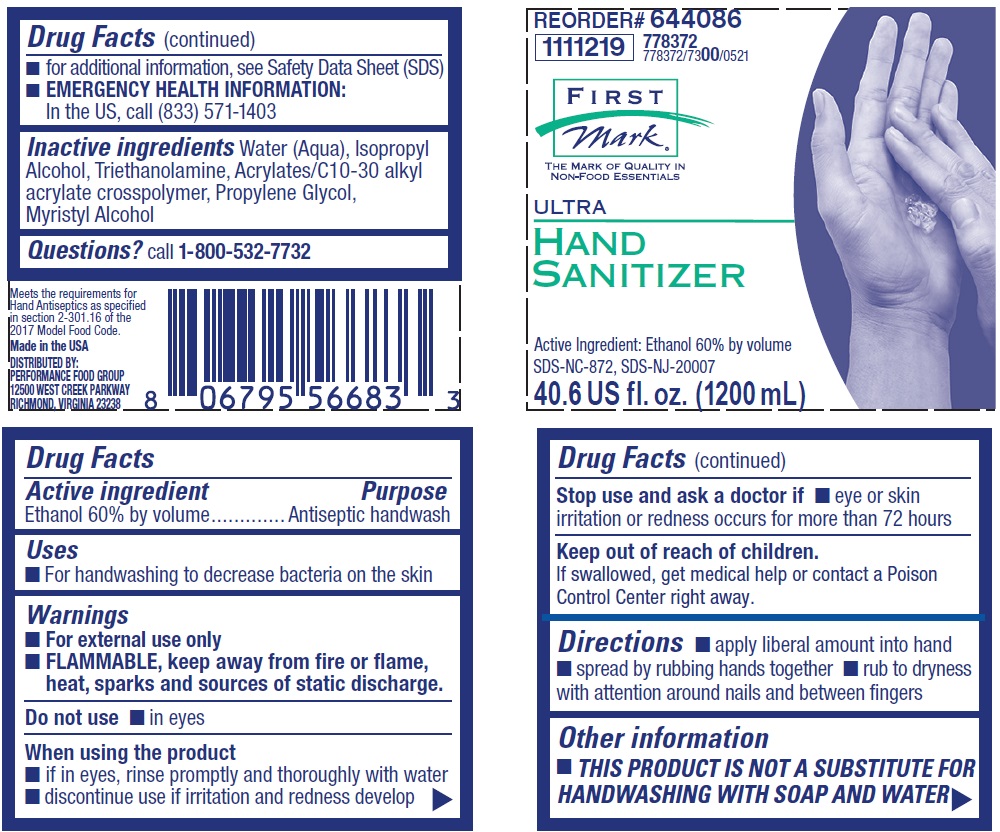 DRUG LABEL: FIRST MARK ULTRA HAND SANITIZER
NDC: 51042-002 | Form: LIQUID
Manufacturer: Performance Food Group
Category: otc | Type: HUMAN OTC DRUG LABEL
Date: 20251230

ACTIVE INGREDIENTS: ALCOHOL 60 mL/100 mL
INACTIVE INGREDIENTS: ISOPROPYL ALCOHOL; WATER; TROLAMINE; CARBOMER COPOLYMER TYPE B (ALLYL PENTAERYTHRITOL CROSSLINKED); PROPYLENE GLYCOL; MYRISTYL ALCOHOL

Drug Facts

Active ingredient

Ethyl Alcohol 60% v/v

Purpose

Antiseptic handwash

Uses

- For handwashing to decrease bacteria on the skin

Warnings

- For external use only
- FLAMMABLE, keep away from fire or flame, heat, sparks and sources of static discharge

Do not use

- In eyes

When using this product

- If in eyes, rinse promptly and thoroughly with water
- Discontinue use if irritation and redness develop

Stop use and ask a doctor if eye or skin irritation or redness occurs for more than 72 hours

Keep out of reach of children. If swallowed, get medical help or contact a Poison Control Center right away.

Directions

- Apply liberal amount into hand
- Spread by rubbing hands together
- Rub to dryness with attention to area around nails and between fingers

Other information

- THIS PRODUCT IS NOT A SUBSTITUTE FOR HANDWASHINGWITH SOAP AND WATER
- For additional information, see Safety Data Sheet (SDS)
- EMERGENCY HEALTH INFORMATION: In the US, call (833) 571-1403

INACTIVE INGREDIENT

Inactive ingredients water (aqua), isopropyl alcohol, triethanolamine, acrylates/C10-30 alkyl acrylate crosspolymer, propylene glycol, myristyl alcohol

Principal display panel and representative label

REORDER # 644086

1111219 778372

778372/7300/0521

FIRST

MARK

The Mark of Quality In

Non-Food Essentials

ULTRA

HAND

SANITIZER

Active Ingredient: Ethanol 60% by volume

SDS-NC-872, SDS-NJ-20007

40.6 US fl. oz. (1200 mL)

Meets the requirements for

Hand Antiseptics as specified

in section 2-301.16 of the

2017 Model Food Code.

Made in the USA

DISTRIBUTED BY:

PERFORMANCE FOOD GROUP

12500 WEST CREEK PARKWAY

RICHMOND, VIRGINIA 23238